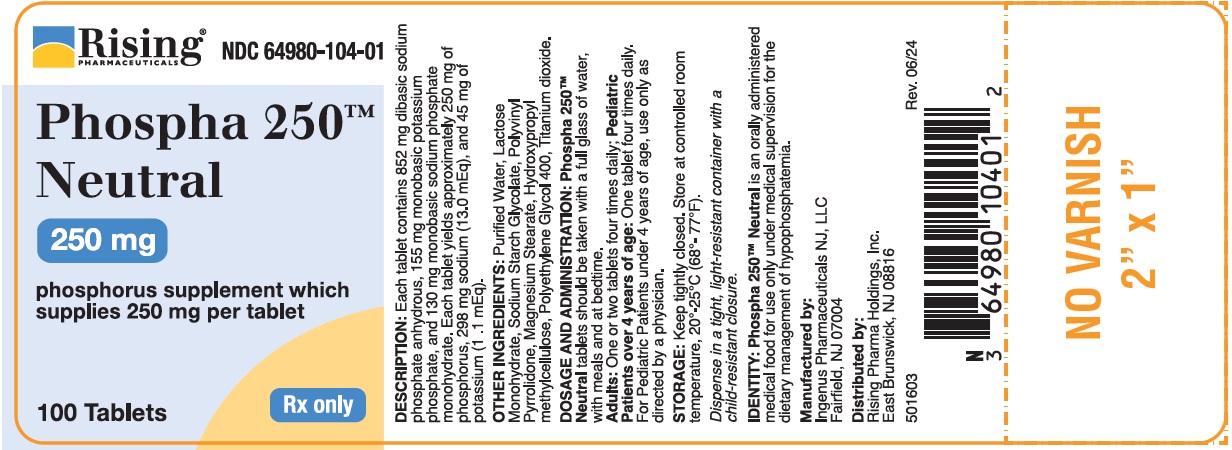 DRUG LABEL: Dibasic Sodium Phosphate, Monobasic Potassium Phosphate and Monobasic Sodium Phosphate
NDC: 64980-104 | Form: TABLET
Manufacturer: Rising Pharma Holdings, Inc.
Category: prescription | Type: Human Prescription Drug Label
Date: 20240805

ACTIVE INGREDIENTS: SODIUM PHOSPHATE, DIBASIC, ANHYDROUS 852 mg/1 1; POTASSIUM PHOSPHATE, MONOBASIC 155 mg/1 1; SODIUM PHOSPHATE, MONOBASIC, MONOHYDRATE 130 mg/1 1
INACTIVE INGREDIENTS: WATER; LACTOSE MONOHYDRATE; SODIUM STARCH GLYCOLATE TYPE A POTATO; POVIDONE K30; MAGNESIUM STEARATE; HYPROMELLOSE 2910 (15000 MPA.S); POLYETHYLENE GLYCOL 400; TITANIUM DIOXIDE

PHOSPHA 250™ NEUTRAL
Supplies 250 mg of phosphorus per tablet

DESCRIPTION

Each tablet contains 852 mg dibasic sodium phosphate anhydrous, 155 mg monobasic potassium phosphate, and 130 mg monobasic sodium phosphate monohydrate. Each tablet yields approximately 250 mg of phosphorus, 298 mg of sodium (13.0 mEq) and 45 mg of potassium (1 .1 mEq).

OTHER INGREDIENTS

Purified Water, Lactose Monohydrate, Sodium Starch Glycolate, Polyvinyl Pyrrolidone, Magnesium Stearate, Hydroxypropyl methylcellulose, Polyethylene Glycol 400, Titanium dioxide.

CLINICAL PHARMACOLOGY

Phosphorus has a number of important functions in the biochemistry of the body. The bulk of the body's phosphorus is located in the bones, where it plays a key role in osteoblastic and osteoclastic activities. Enzymatically catalyzed phosphate-transfer reactions are numerous and vital in the metabolism of carbohydrate, lipid and protein, and a proper concentration of the anion is of primary importance in assuring an orderly biochemical sequence. ln addition, phosphorus plays an important role in modifying steady-state tissue concentrations of calcium. Phosphate ions are important buffers of the intracellular fluid, and also play a primary role in the renal excretionof the hydrogen ion.

Oral administration of inorganic phosphates increases serum phosphate levels. Phosphates lower urinary calcium levels in idiopathic hypercalciuria.

In general, in adults, about two thirds of the ingested phosphate in absorbed from the bowel, most of which is rapidly excreted into the urine.

INDICATIONS AND USAGE

PHOSPHA 250TM NEUTRAL increases urinary phosphate and pyrophosphate. As a phosphorus supplement, each tablet supplies 25% of the U.S. Recommended Daily Allowance (U.S. RDA) of phosphorus for adults and children over 4 years of age.

CONTRAINDICATIONS

This product is contraindicated in patients with infected phosphate stones, in patients with severely impaired renal function (less than 30% of normal) and in the presence of hyperphosphatemia.

PRECAUTIONS

GENERAL PRECAUTIONS

General: This product contains potassium and sodium and should be used with caution if regulation of these elements is desired. Occasionally, some individuals may experience a mild laxative effect during the first few days of phosphate therapy. If laxation persists to an unpleasant degree reduce the daily dose until this effect subsides or, if necessary, discontinue the use of the product.

Caution should be exercised when prescribing this product in the following conditions: Cardiac disease (particularly in digitalized patients); severe adrenal insufficiency (Addison's disease); acute dehydration; severe renal insufficiency; renal function impairment or chronic renal disease; extensive tissue breakdown (such as severe burns); myotonia congenita; cardiac failure; cirrhosis of the liver or severe hepatic disease; peripheral or pulmonary edema; hypernatremia; hypertension; toxemia of pregnancy; hypoparathyroidism; and acute pancreatitis. Rickets may benefit from phosphate therapy, but caution should be exercised. High serum phosphate levels may increase the incidence of extraskeletal calcification.

PATIENT COUNSELING INFORMATION

Information for Patients: Patients with kidney stones may pass old stones when phosphate therapy is started and should be warned of this possibility. Patients should be advised to avoid the use of antacids containing aluminum, magnesium, or calcium which may prevent the absorption of phosphate.

LABORATORY TESTS

Laboratory: Careful monitoring of renal function and serum calcium, phosphorus, potassium, and sodium may be required at periodic intervals during phosphate therapy. Other tests may be warranted in some patients, depending on conditions.

Drug Interactions:

The use of antacids containing magnesium, aluminum, or calcium in conjunction with phosphate preparations may bind the phosphate and prevent its absorption. Concurrent use of antihypertensives, especially diazoxide, guanethidine, hydralazine, methyldopa, or rauwolfia alkaloid; or corticosteroids, especially mineralocorticoids or corticotropin with sodium phosphate may result in hypernatremia. Calcium-containing preparations and/or Vitamin D may antagonize the effects of phosphates in the treatment of hypercalcemia. Potassium-containing medication or potassium-sparing diuretics may cause hyperkalemia. Patients should have serum potassium level determinations at periodic intervals.

Carcinogenesis, Mutagenesis, Impairment of Fertility:

No long term or reproduction studies in animals or humans have been performed with PHOSPHA 250TM NEUTRAL to evaluate its carcinogenic, mutagenic, or impairment of fertility potential.

Pregnancy:

Teratogenic Effects. Pregnancy Class C. Animal reproduction studies have not been conducted with PHOSPHA 250 TM NEUTRAL. It is also not known whether this product can cause fetal harm when administered to a pregnant woman or can affect reproductive capacity.

This product should be given to a pregnant woman only if clearly needed.

Nursing Mothers:

It is not known whether this drug is excreted in human milk. Because many drugs are excreted in human milk, caution should be exercised when this product is administered to a nursing woman.

Pediatric Use:

See DOSAGE AND ADMINISTRATION.

ADVERSE REACTIONS:

Gastrointestinal upset (diarrhea, nausea, stomach pain, and vomiting) may occur with phosphate therapy. Also, bone and joint pain (possible phosphate-induced osteomalacia) could occur. The following adverse effects may be observed (primarily from sodium or potassium): headaches; dizziness; mental confusion; seizures; weakness or heaviness of legs; unusual tiredness or weakness; muscle cramps; numbness, tingling, pain or weakness of hands or feet; numbness or tingling around lips; fast or irregular heartbeat; shortness of breath or troubled breathing; swelling of feet or lower legs; unusual weight gain; low urine output; unusual thirst.

To report SUSPECTED ADVERSE REACTIONS, contact Rising Pharma Holdings, Inc., at 1-844-874-7464 or FDA at 1-800-FDA-1088 or www.fda.gov/medwatch.

DOSAGE AND ADMINISTRATION

PHOSPHA 250TM NEUTRAL tablets should be taken with a full glass of water, with meals and at bedtime.

Adults: One or two tablets, four times daily;

Pediatric patients over 4 years of age: One tablet four times daily.

Pediatric Patients under 4 years of age: Use only as directed by physician.

HOW SUPPLIED

White, film-coated, capsule-shaped tablet, debossed with RIS 104 on each tablet.

NDC #64980-104-01
Bottles of 100 tablets

STORAGE

Keep tightly closed. Store at controlled room temperature 20°-25°C (68°-77°F}. Dispense in tight, light-resistant containers with child resistant closures.

IDENTITY: Phospha 250TM Neutral

is an orally administered medical food for use only under medical supervision for the dietary management of hypophosphatemia.

Manufactured by:
Ingenus Pharmaceuticals NJ, LLC
Fairfield, NJ 07004
Distributed by:
Rising Pharma Holdings, Inc.
East Brunswick, NJ 08816
Rx only
550303 Rev: 07/2024

PACKAGE LABEL.PRINCIPAL DISPLAY - 250 mg
Rising® NDC 64980-104-01

Phospha 250TM
Neutral

phosphourus supplement which
supplies 250 mg per tablet

100 Tablets

Rx Only